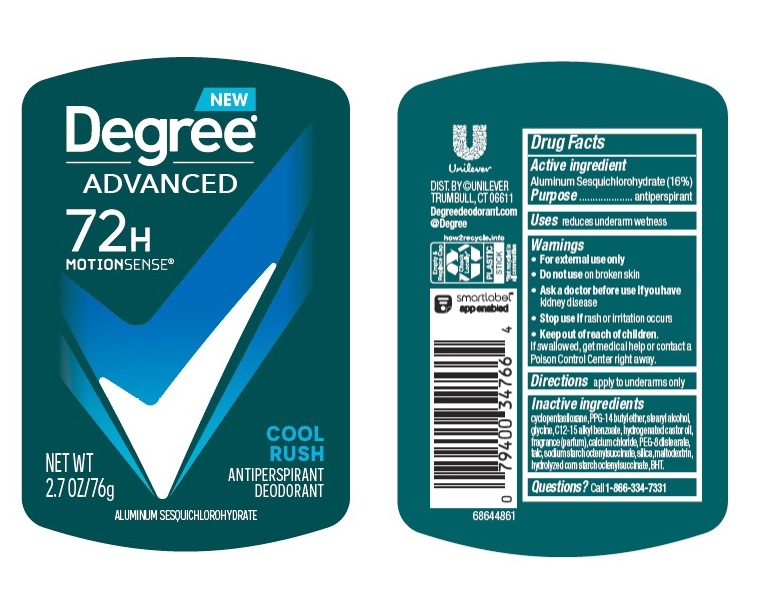 DRUG LABEL: Degree
NDC: 64942-1933 | Form: STICK
Manufacturer: Conopco Inc. d/b/a/ Unilever
Category: otc | Type: HUMAN OTC DRUG LABEL
Date: 20250513

ACTIVE INGREDIENTS: ALUMINUM SESQUICHLOROHYDRATE 16 g/100 g
INACTIVE INGREDIENTS: GLYCINE; ALKYL (C12-15) BENZOATE; HYDROGENATED CASTOR OIL; CALCIUM CHLORIDE; CYCLOMETHICONE 5; BUTYLATED HYDROXYTOLUENE; MALTODEXTRIN; PEG-8 DISTEARATE; TALC; SILICON DIOXIDE; PPG-14 BUTYL ETHER; STEARYL ALCOHOL

Degree Advanced Cool Rush 72H Antiperspirant Deodorant

Drug Facts

Active ingredient

Aluminum Sesquichlorohydrate (16%)

Purpose

antiperspirant

Uses

reduces underarm wetness

Warnings

• For external use only.
• Do not use on broken skin .
• Ask a doctor before use if you have kidney disease.
• Stop use if rash or irritation occurs.

• Keep out of reach of children.

If swallowed, get medical help or contact a Poison Control Center right away.

Directions

apply to underarms only

Inactive ingredients

Cyclopentasiloxane, PPG-14 Butyl Ether, Stearyl Alcohol, Glycine, C12-15 Alkyl Benzoate, Hydrogenated Castor Oil, Fragrance (Parfum), Calcium Chloride, PEG-8 Distearate, Talc, Sodium Starch Octenylsuccinate, Silica, Maltodextrin, Hydrolyzed Corn Starch Octenylsuccinate, BHT.

Questions?

Call toll-free 1-866-334-7331